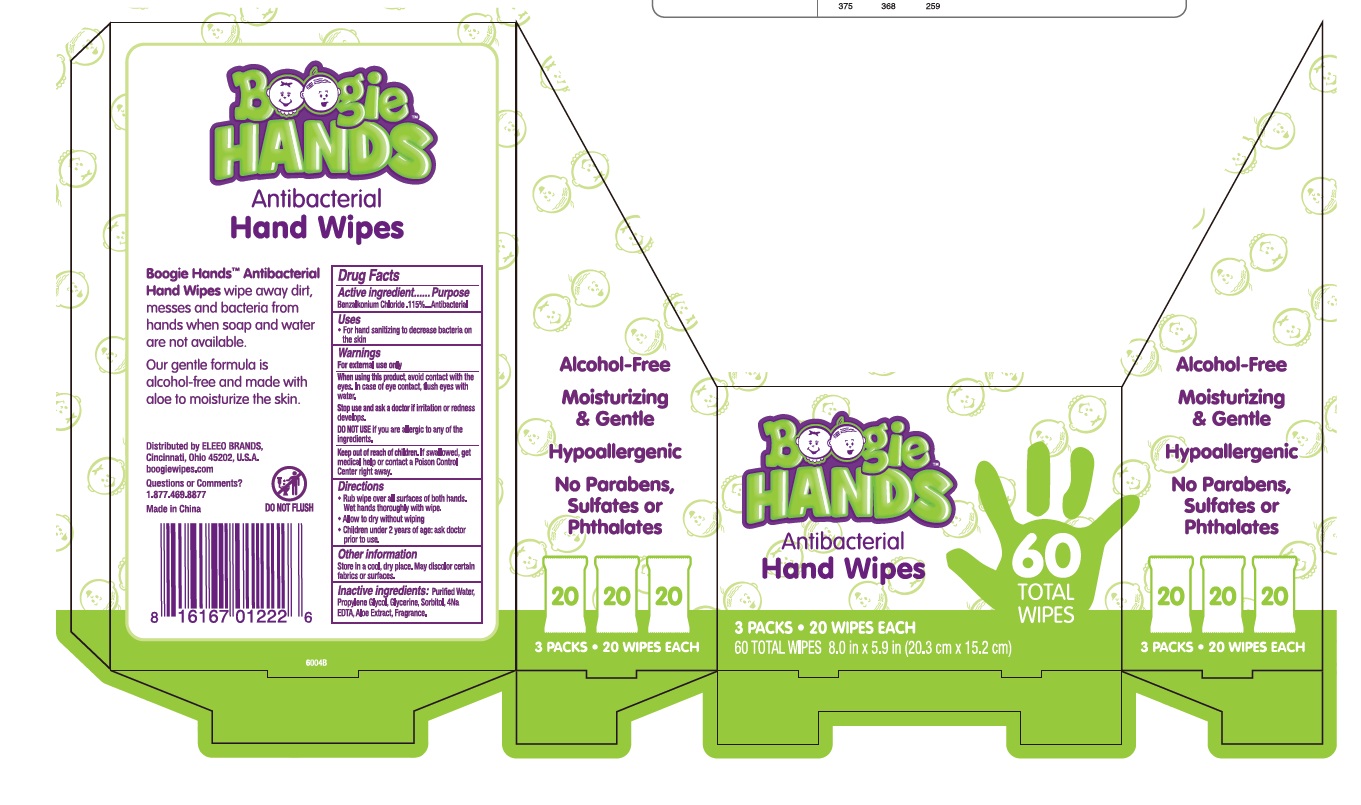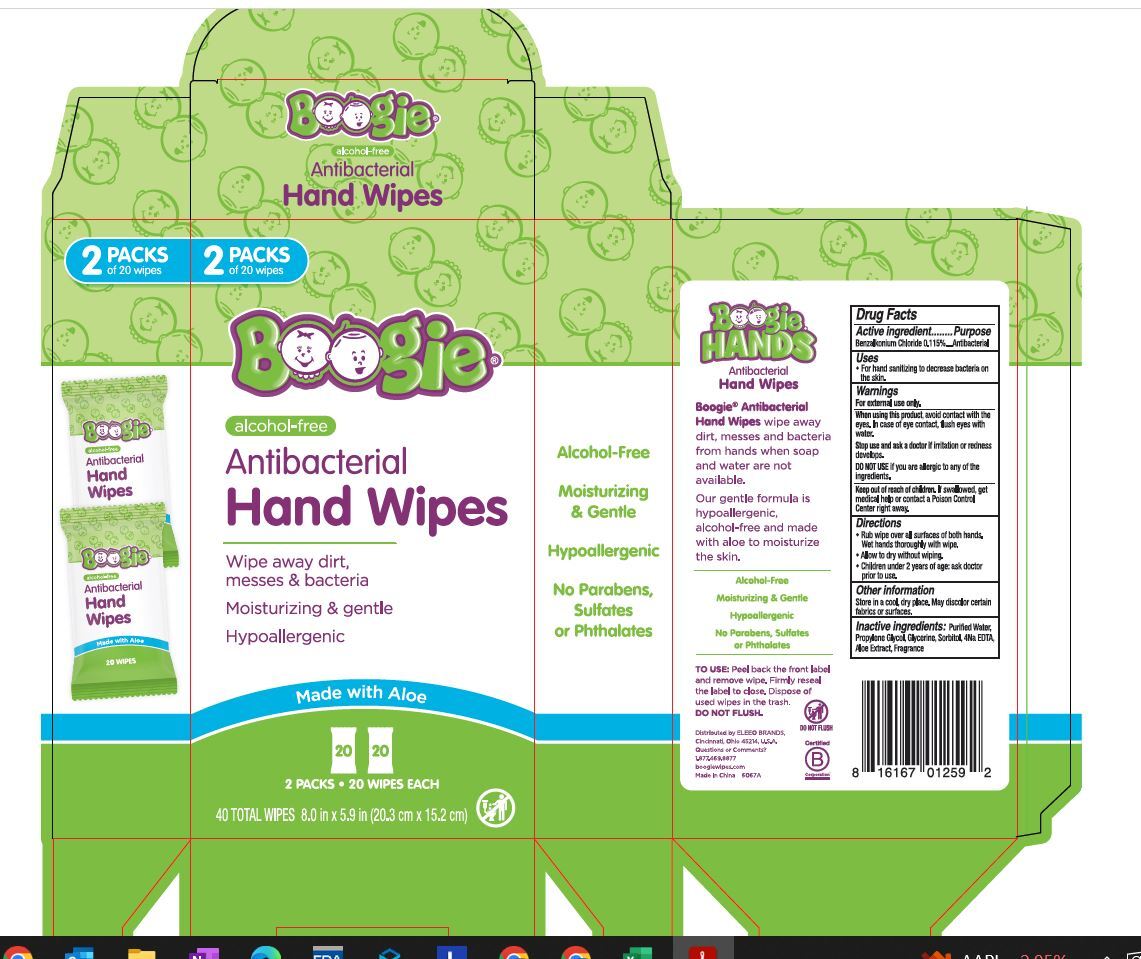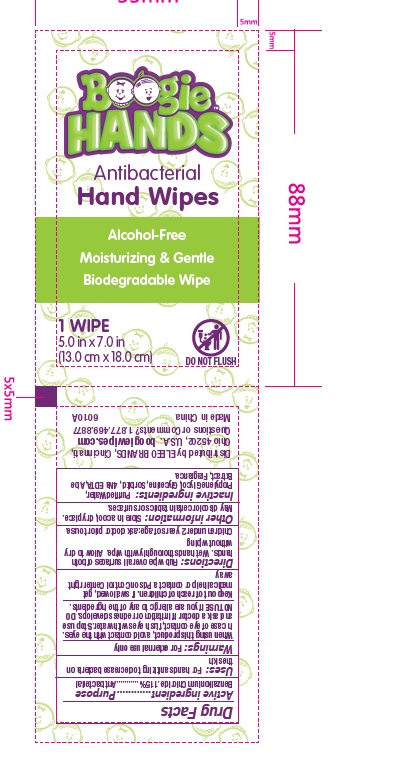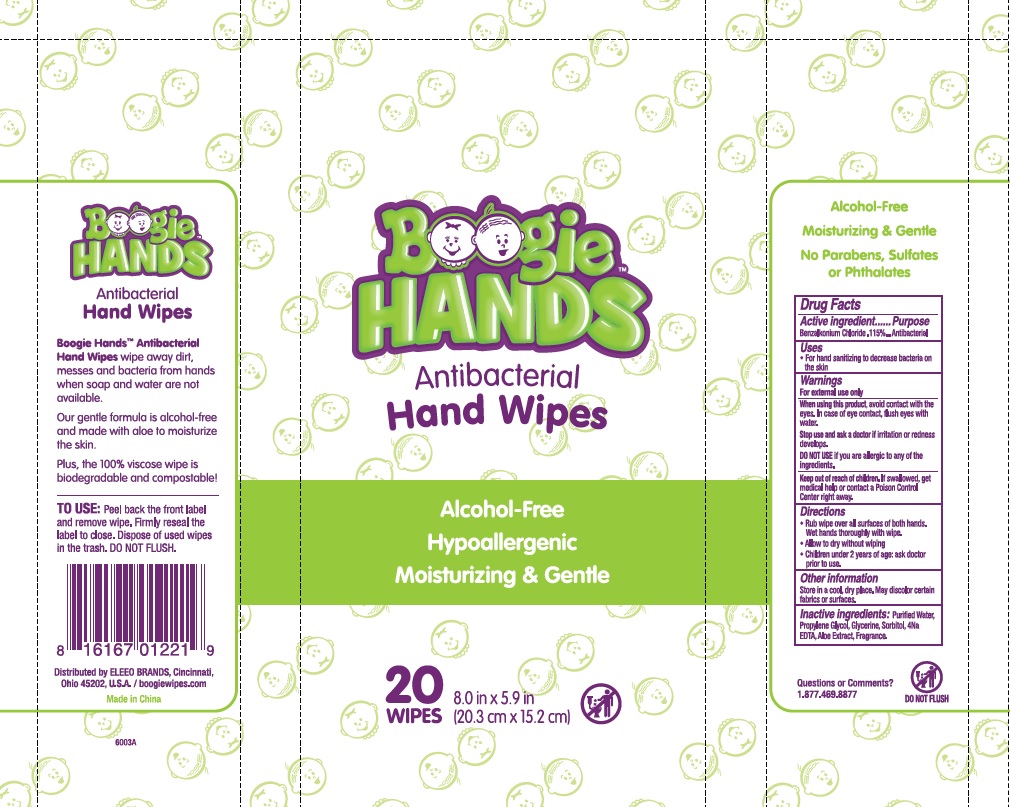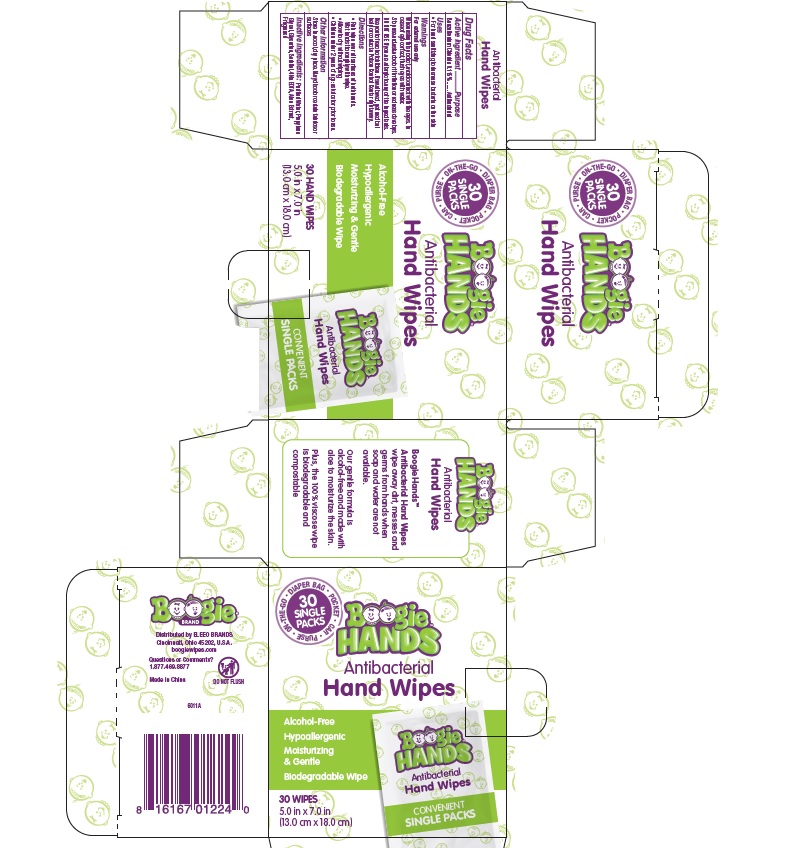 DRUG LABEL: Boogie Hands Antibacterial Wet Wipes
NDC: 79747-007 | Form: CLOTH
Manufacturer: ELEEO BRANDS LLC
Category: otc | Type: HUMAN OTC DRUG LABEL
Date: 20250930

ACTIVE INGREDIENTS: BENZALKONIUM CHLORIDE 0.0012 g/100 mL
INACTIVE INGREDIENTS: WATER; GLYCERIN; PROPYLENE GLYCOL; SORBITOL; ALOE VERA LEAF; EDETATE SODIUM

Boogie Hands Antibacterial Hand Wipes

Active ingredients

Benalkonium chloride (0.115%)

Purpose

Antibacterial

Use

For hand sanitizing to decrease bacteria on skin

Warnings

For external use only

Do Not Use

if you are allergic to any of the ingredients

When using this product

donot get into eyes.

if contact occurs, rinse thoroughly with water.

Stop use and ask a doctor if

irritation or rash develops.

and continues for more than 72 hours

Keep out of reach of children.

If swallowed, get medical help or contact a Poison Control Center right away

Directions:

*adults and children 2 years and over

- apply to hands
- allow to dry without wiping

*children under 2 years

- ask a doctor before use

Inactive ingredients

Water, Gycerin, Fragrance, Aloe extract, Disodium EDTA , Propylene Glycol, Sorbitol